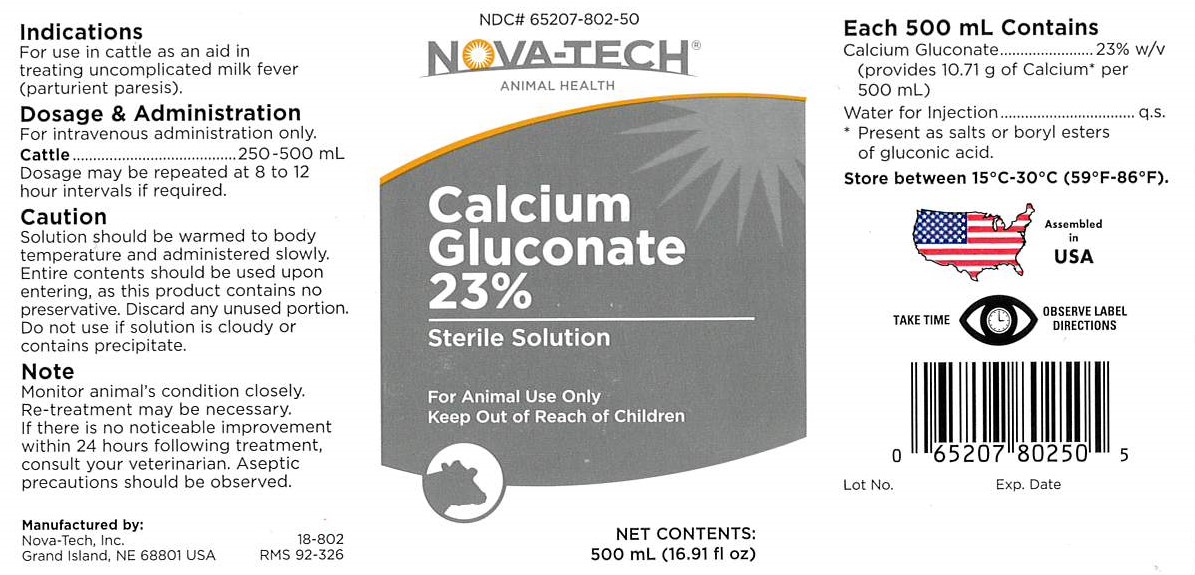 DRUG LABEL: Calcium Gluconate
NDC: 65207-802 | Form: INJECTION, SOLUTION
Manufacturer: Nova-Tech, Inc.
Category: animal | Type: OTC ANIMAL DRUG LABEL
Date: 20200319

ACTIVE INGREDIENTS: CALCIUM GLUCONATE 23 g/100 mL

CALCIUM GLUCONATE 23%

INDICATIONS

For use in cattle as an aid in treating uncomplicated milk fever (parturient paresis).

DOSAGE & ADMINISTRATION

For intravenous administration only.

Cattle ........... 250-500 mL

Dosage may be repeated at 8 to 12 hour intervals if required.

PRECAUTIONS

TAKE TIME OBSERVE LABEL DIRECTIONS

INFORMATION FOR OWNERS/CAREGIVERS

Manufactured by:

Nova-Tech Inc.

Grand Island, NE 68801 USA

18-802

RMS 92-326

NDC# 65207-802-50

Nova-Tech® Animal Health

Calcium Gluconate 23%

Sterile Solution

Net Contents:

500 mL (16.91 fl oz)

Assembled in USA

Lot No.

Exp. Date

Each 500 mL Contains

Calcium Gluconate ............................. 23% w/v

(provides 10.71 g of Calcium* per 500 mL)

Water for Injection ............................ q.s.

*Present as salts or boryl esters of gluconic acid.

STORAGE AND HANDLING

Store between 15°C-30°C (59°F-86°F).

GENERAL PRECAUTIONS

FOR ANIMAL USE ONLY

KEEP OUT OF REACH OF CHILDREN